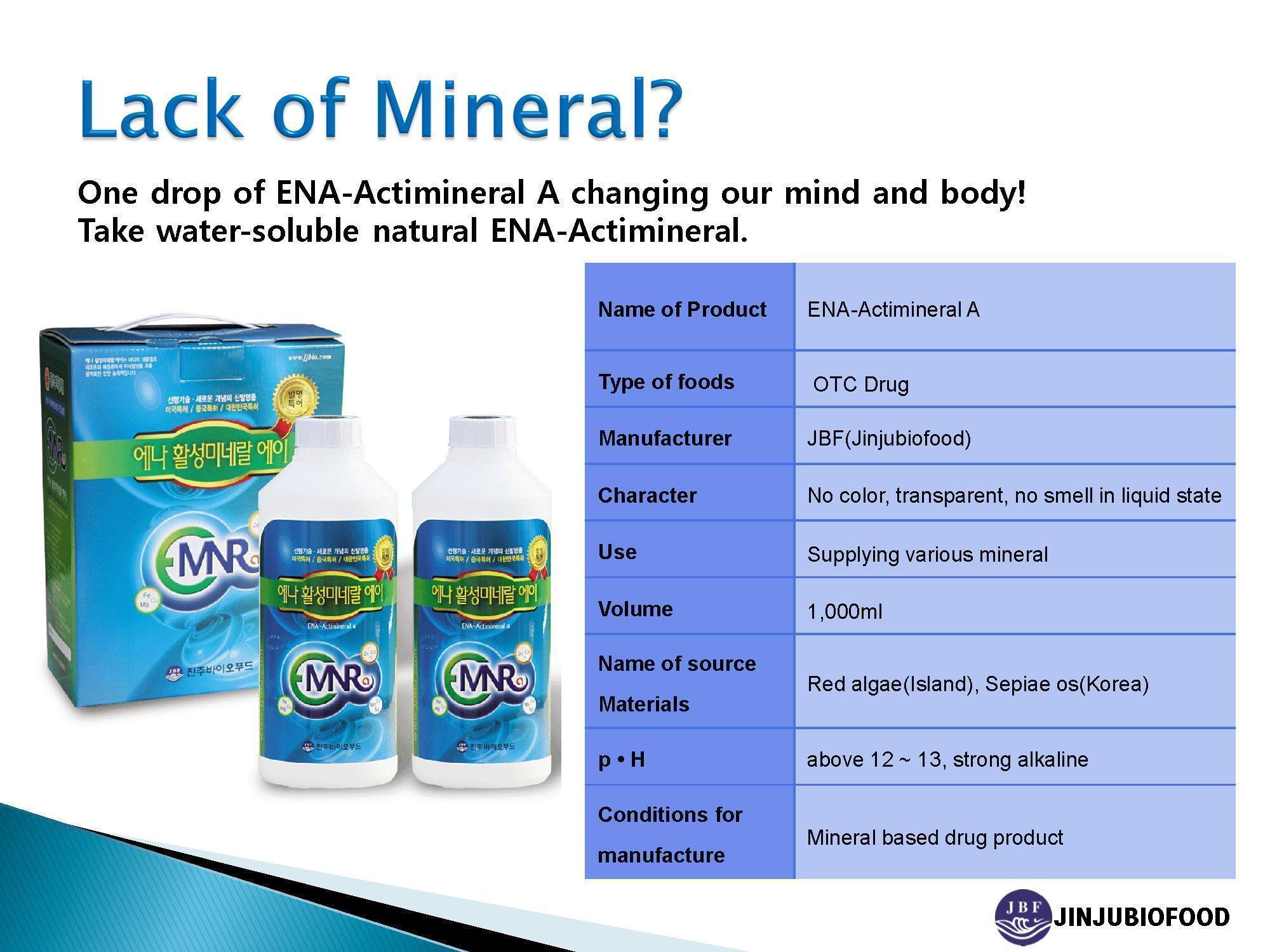 DRUG LABEL: ENA Actimineral A
NDC: 58543-1001 | Form: LIQUID
Manufacturer: Jinju Bio Food
Category: otc | Type: HUMAN OTC DRUG LABEL
Date: 20130628

ACTIVE INGREDIENTS: CALCIUM 803.8 mg/1000 mL
INACTIVE INGREDIENTS: IRON; ZINC; MAGNESIUM; POTASSIUM; COPPER; SODIUM

Drug Facts

ACTIVE INGREDIENT

calcium

INACTIVE INGREDIENT

iron, zinc, magnesium, sodium, potassium, copper

PURPOSE

supplying various minerals to human body

keep out or reach of the children

INDICATIONS AND USAGE

- It is thick alkaline solution of above pH12, so please dilute with mineral water when in use.
- Please dilute about 2ml~100ml similar with 1~5 lids of bottle in 1~2L and drink often.
- Mineral precipitate might be seen depending on storage state, so please shake and drink

WARNINGS

avoid contact with eyes

DOSAGE AND ADMINISTRATION

for external use only